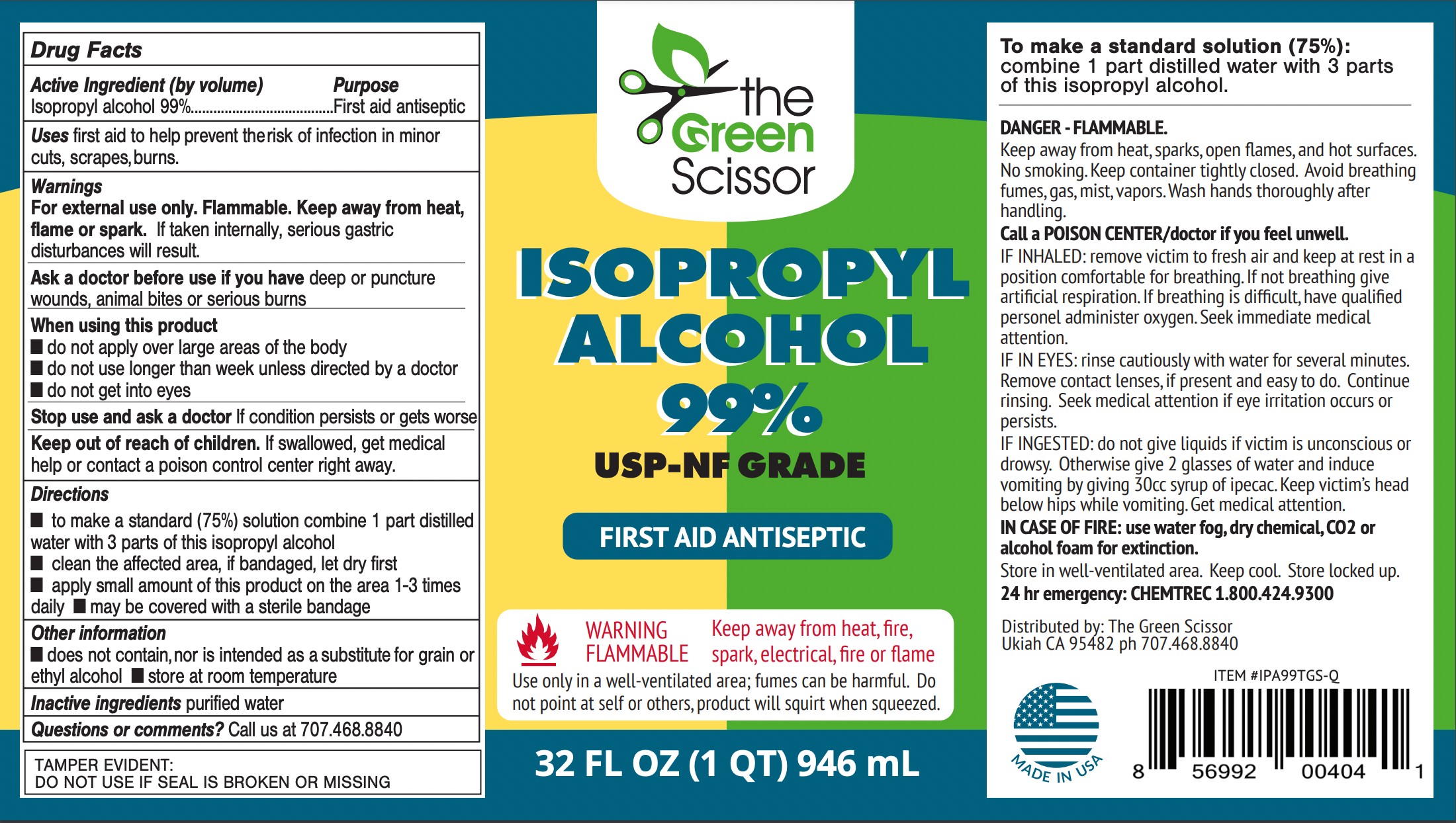 DRUG LABEL: The Green Scissor
NDC: 81893-111 | Form: LIQUID
Manufacturer: The Green Scissor Inc
Category: otc | Type: HUMAN OTC DRUG LABEL
Date: 20251203

ACTIVE INGREDIENTS: ISOPROPYL ALCOHOL 99 mL/100 mL
INACTIVE INGREDIENTS: WATER

Green Scissor Quart 99% Isopropyl

Active Ingredient(s)

Isopropyl Alcohol 99% v/v. Purpose: First aid antiseptic

Purpose

First Aid Antiseptic

Use

first aid to help prevent the risk of infection in minor cuts, scrapes, burns.

Warnings

For external use only. Flammable. Keep away from heat, flame, or spark. If taken internally, serious gastric disturbances will result.

Ask a doctor before use if you have

deep or puncture wounds, animal bites or serious burns

When using this product

do not get into eyes
do not apply over the large areas of the body
do not use longer than week unless directed by a doctor

STOP USE

If condition persists or gets worse.

Keep out of reach of children. If swallowed, get medical help or contact a Poison Control Center right away.

Directions

- To make a standard solution (75%) combine one part of distilled water with three parts of this isopropyl alcohol
- clean the affected area; if bandaged, let it dry first
- Apply a small amount of this product in an area 1-3 times daily
- may be covered with a sterile bandage

Other information

store at room temperature

does not contain, nor is intended as a substitute for grain or ethyl alcohol

Inactive ingredients

purified water

Package Label - Principal Display Panel

946 ml NDC: 81893-111-21